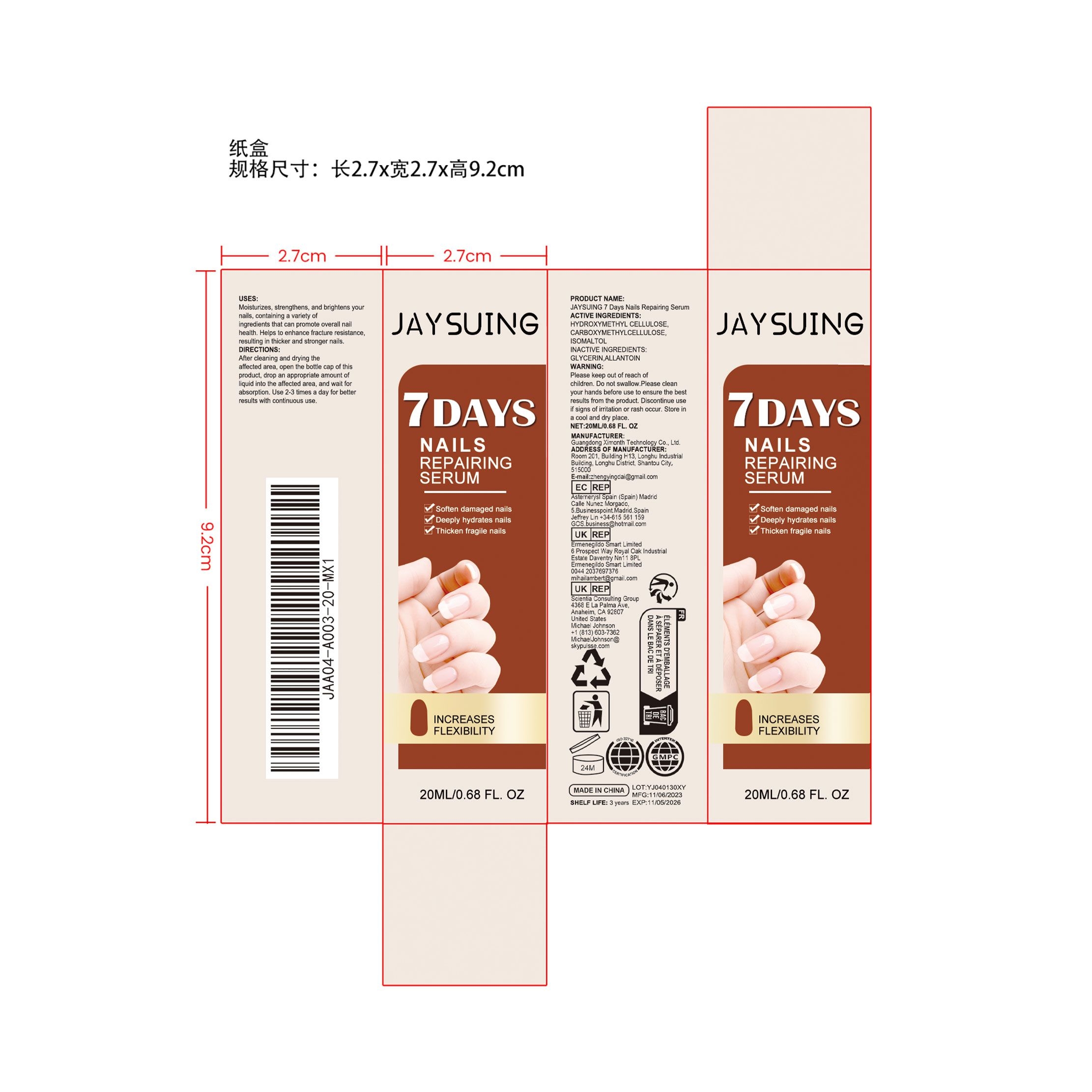 DRUG LABEL: JAYSUING 7 Days Nails Repairing Serum
NDC: 84660-057 | Form: LIQUID
Manufacturer: Guangdong Ximonth Technology Co., Ltd.
Category: otc | Type: HUMAN OTC DRUG LABEL
Date: 20241101

ACTIVE INGREDIENTS: ISOMALTOL 3 mg/20 mg; HYDROXYMETHYL CELLULOSE 6 mg/20 mg; CARBOXYMETHYLCELLULOSE 2 mg/20 mg
INACTIVE INGREDIENTS: ALLANTOIN 6 mg/20 mg; GLYCERIN 3 mg/20 mg

ACTIVE INGREDIENTS

HYDROXYMETHYL CELLULOSE,CARBOXYMETHYLCELLULOSE,ISOMALTOL

PURPOSE

Moisturizes, strengthens, and brightens your nails, containing a variety of ingredients that can promote overall nail health. Helps to enhance fracture resistance, resulting in thicker and stronger nails.

USES

After cleaning and drying the affected area, open the bottle cap of this product, drop an appropriate amount of liquid into the affected area, and wait for absorption. Use 2-3 times a day for better results with continuous use.

WARNING

Please keep out of reach of children. Do not swallow.Please clean your hands before use to ensure the best results from the product. Discontinue use if signs of irritation or rash occur. Store in a cool and dry place.

STOP USE

Discontinue use if signs of irritation or rash occur.

DO NOE USE

Discontinue use if signs of irritation or rash occur.

KEEP OUT OF REACH OF CHILDREN

Please keep out of reach of children. Do not swallow.

STORAGE AND HANDLING

Store in a cool and dry place.

INACTIVE INGREDIENT

GLYCERIN,ALLANTOIN